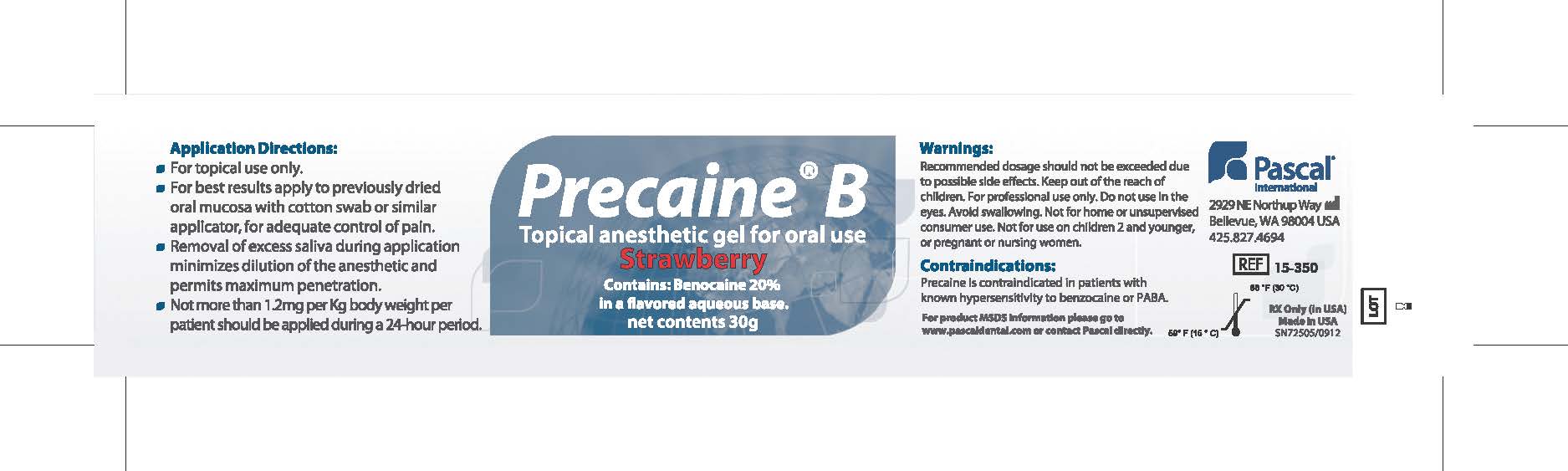 DRUG LABEL: Precaine B
NDC: 10866-0087 | Form: GEL
Manufacturer: Pascal Company, Inc.
Category: prescription | Type: HUMAN PRESCRIPTION DRUG LABEL
Date: 20221219

ACTIVE INGREDIENTS: BENZOCAINE 221 mg/1 g

Precaine B

Directoons

Application Directions:

For topical use only

For best results apply to previously dried oral mucosa with cotton swab or similar applicator for adequate control of pain

Removal of excess saliva during application minimizes dilution of the anesthetic and perimts maximum penetration

Not more than 1.2mg per Kg body weight per patient should be applied during a 24-hour period

Warnings

Warning:

Recommended dosage should not be exceeded due to possible side effects. Keep out of the reach of children. For professional use only. Do not use in the eyes. Avoid swallowing. Not for home or unsupervised consumer use. Not for use on children 2 and younger or pregnant or nursing women.

Contraindications

Precaine is contraindicated in patients with known hypersensitivity to benzocaine or PABA.

Other Information

For product MSDS information, please go to www.pascaldental.com or contact Pascal directly

Store product between 60 degress F (16 degress C) and 86 degrees F (30 degress C)

Rx only in USA

Made in USA

Precaine B

Topical Anesthetic Gel for oral use

Strawberry

Contain: Benzocaine 20% in a flavored aqueous base

Net Contents 30g

Pascal International

2929 NE Northup Way

Bellevue, WA 98004

425.827.4694

REF 15-350

SN72505/0912